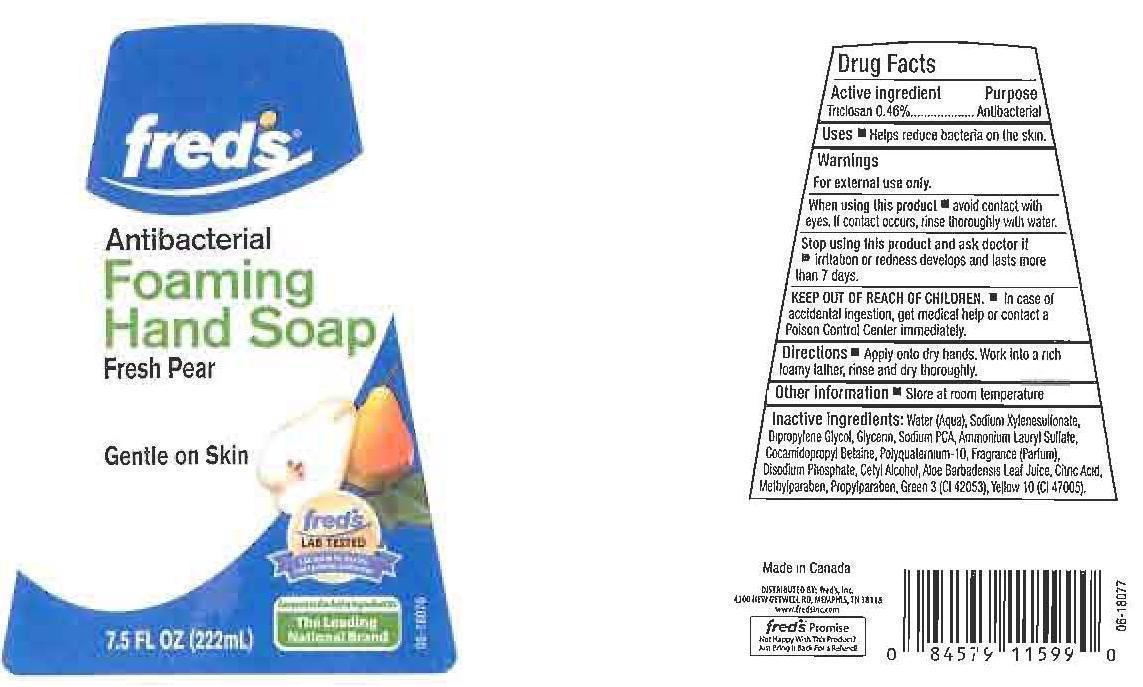 DRUG LABEL: FREDS
NDC: 55315-185 | Form: LIQUID
Manufacturer: FREDS INC.
Category: otc | Type: HUMAN OTC DRUG LABEL
Date: 20120925

ACTIVE INGREDIENTS: TRICLOSAN 0.46 mg/100 mL
INACTIVE INGREDIENTS: WATER; SODIUM XYLENESULFONATE; DIPROPYLENE GLYCOL; GLYCERIN; SODIUM PYRROLIDONE CARBOXYLATE; AMMONIUM LAURYL SULFATE; COCAMIDOPROPYL BETAINE; POLYQUATERNIUM-10 (400 CPS AT 2%); SODIUM PHOSPHATE, DIBASIC ANHYDROUS; CETYL ALCOHOL; ALOE VERA LEAF; CITRIC ACID MONOHYDRATE; METHYLPARABEN; PROPYLPARABEN; FD&C GREEN NO. 3; D&C YELLOW NO. 10

DRUG FACTS

ACTIVE INGREDIENT

TRICLOSAN 0.46%

PURPOSE

ANTIBACTERIAL

USES

HELPS REDUCE BACTERIA ON THE SKIN.

WARNINGS

FOR EXTERNAL USE ONLY.

WHEN USING THIS PRODUCT

STOP USING THIS PRODUCT AND ASK DOCTOR IF

KEEP OUT OF REACH OF CHILDREN

IN CASE OF ACCIDENTAL INGESTION, GET MEDICAL HELP OR CONTACT A POISON CONTROL CENTER IMMEDIATELY.

DIRECTIONS

APPLY ONTO DRY HANDS. WORK INTO A RICH FOAMY LATHER, RINSE AND DRY THOROUGHLY.

OTHER INFORMATION

STORE AT ROOM TEMPERATURE.

INACTIVE INGREDIENTS:

WATER (AQUA), SODIUM XYLENESULFONATE, DIPROPYLENE GLYCOL, GLYCERIN, SODIUM PCA, AMMONIUM LAURYL SULFATE, COCAMIDOPROPYL BETAINE, POLYQUATERNIUM-10, FRAGRANCE (PARFUM), DISODIUM PHOSPHATE, CETYL ALCOHOL, ALOE BARBADENSIS LEAF JUICE, CITRIC ACID, METHYLPARABEN, PROPYLPARABEN, GREEN 3 (CI 42053), YELLOW (CI 47005).